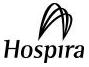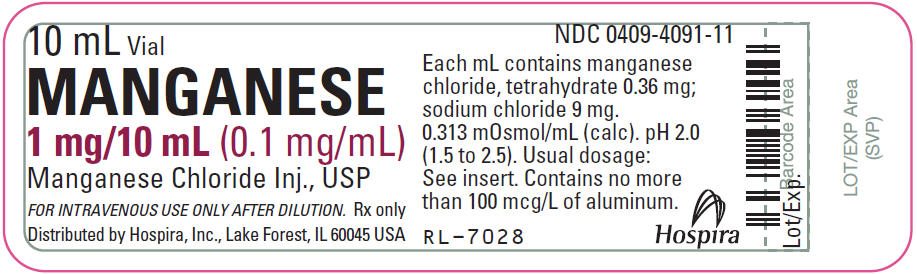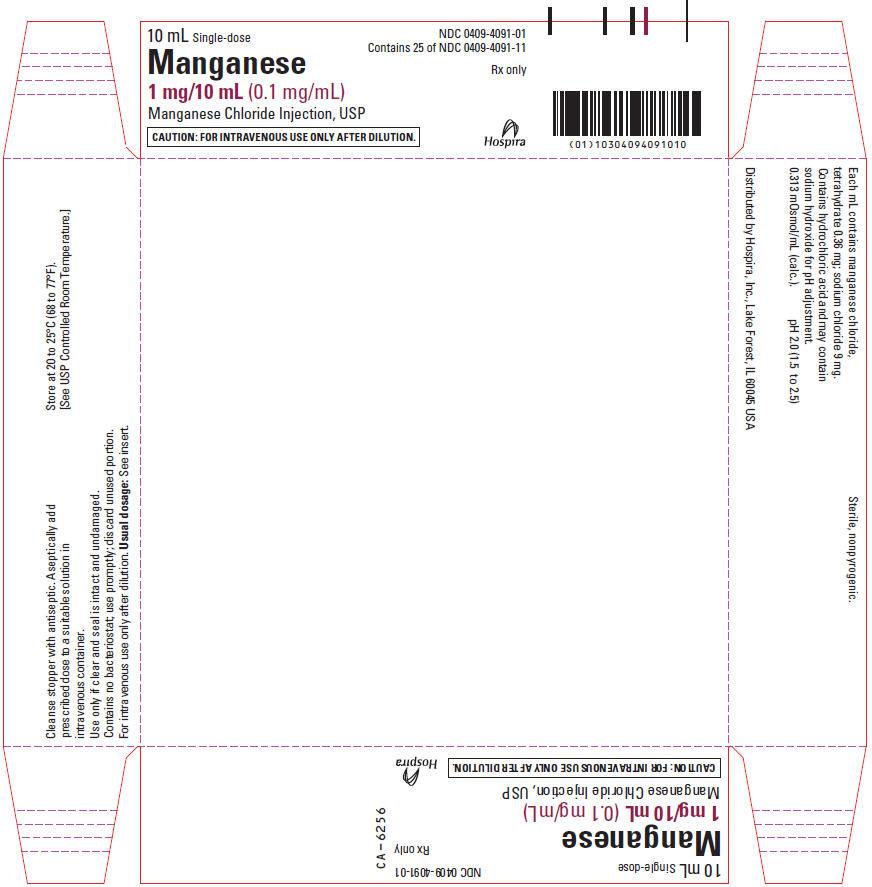 DRUG LABEL: MANGANESE
NDC: 0409-4091 | Form: INJECTION, SOLUTION
Manufacturer: Hospira, Inc.
Category: prescription | Type: HUMAN PRESCRIPTION DRUG LABEL
Date: 20241017

ACTIVE INGREDIENTS: MANGANESE CHLORIDE 0.1 mg/1 mL
INACTIVE INGREDIENTS: SODIUM CHLORIDE 9 mg/1 mL; HYDROCHLORIC ACID; SODIUM HYDROXIDE; WATER

Manganese
0.1 mg/mL

Manganese Chloride
Injection, USP

FOR I.V. USE ONLY AFTER DILUTION
Plastic Vial

Rx only

DESCRIPTION

Manganese 0.1 mg/mL (Manganese Chloride Injection, USP) is a sterile, nonpyrogenic solution intended for use as an additive to intravenous solutions for total parenteral nutrition (TPN). Each mL of solution contains 0.36 mg manganese chloride, tetrahydrate and 9 mg sodium chloride. The solution contains no bacteriostat, antimicrobial agent or added buffer. The pH is 2.0 (1.5 to 2.5); product may contain hydrochloric acid and sodium hydroxide for pH adjustment. The osmolarity is 0.313 mOsmol/mL (calc.).

Manganese Chloride, USP is chemically designated manganese chloride, tetrahydrate (MnCl2 • 4H2O), a deliquescent, crystalline compound soluble in water.

Sodium Chloride, USP is chemically designated NaCl, a white, crystalline compound freely soluble in water.

The semi-rigid vial is fabricated from a specially formulated polyolefin. It is a copolymer of ethylene and propylene. The safety of the plastic has been confirmed by tests in animals according to USP biological standards for plastic containers. The small amount of water vapor that can pass through the plastic container wall will not significantly alter the drug concentration.

CLINICAL PHARMACOLOGY

Manganese is an essential nutrient which serves as an activator for enzymes such as polysaccharide polymerase, liver arginase, cholinesterase and pyruvate carboxylase. Providing manganese during TPN helps prevent development of deficiency symptoms such as nausea and vomiting, weight loss, dermatitis and changes in growth and color of hair.

Under conditions of minimal intake, 20 mcg manganese/day is retained. Manganese is bound to a specific transport protein, transmanganin, a beta-l-globulin. Manganese is widely distributed but concentrates in the mitochondria rich tissues such as brain, kidney, pancreas, and liver. Assays for manganese in whole blood result in concentrations ranging from 6 to 12 mcg/manganese/liter.

Excretion of manganese occurs mainly through the bile, but in the event of obstruction, ancillary excretion routes include pancreatic juice, or return into the lumen of the duodenum, jejunum, or ileum. Urinary excretion of manganese is negligible.

INDICATIONS AND USAGE

Manganese 0.1 mg/mL (Manganese Chloride Injection, USP) is indicated for use in adult patients as a supplement to intravenous solutions given for TPN.

Administration helps to maintain manganese serum levels and to prevent depletion of endogenous stores and subsequent deficiency symptoms.

CONTRAINDICATIONS

None known.

WARNINGS

Direct intramuscular or intravenous injection of Manganese 0.1 mg/mL (Manganese Chloride Injection, USP) is contraindicated as the acidic pH of the solution (pH 2.0) may cause considerable tissue irritation.

Neurologic Toxicity with Manganese

Manganese accumulation in the basal ganglia has been reported in adult and pediatric patients on long‑term parenteral nutrition receiving manganese at higher than recommended dosages and in association with cholestatic liver disease. Brain MRI findings and clinical symptoms have also been observed in patients who received manganese at or below the recommended dosage and with normal blood manganese concentrations. Some adult patients with brain MRI findings reportedly experienced neuropsychiatric symptoms, including changes in mood or memory, seizures and/or parkinsonian‑like tremors, dysarthria, mask-face, and halting gait. Some pediatric patients experienced dystonic movements or seizures. Regression of symptoms and MRI findings have occurred over weeks to months following discontinuation of manganese in most patients but have not always completely resolved.

Monitor patients receiving parenteral nutrition solutions containing manganese for neurologic signs and symptoms and routinely measure whole blood manganese concentrations and liver tests. In case of suspected manganese toxicity or new neuropsychiatric manifestations, temporarily discontinue manganese, check manganese whole blood concentrations, and consider brain MRI evaluation.

Hepatic Accumulation of Manganese

Manganese is primarily eliminated in the bile and excretion is decreased in patients with cholestasis and/or cirrhosis. Hepatic accumulation of manganese has been reported in autopsies of patients receiving long-term parenteral nutrition containing manganese at dosages higher than recommended. Patients with cholestasis and/or cirrhosis receiving parenteral nutrition are at increased risk of manganese brain deposition and neurotoxicity. If a patient develops signs or symptoms of hepatobiliary disease during the use of this drug product, obtain manganese whole blood concentrations; consider discontinuing manganese supplementation in these patients until a full clinical evaluation is completed.

Aluminum Toxicity

This product contains aluminum that may be toxic. Aluminum may reach toxic levels with prolonged parenteral administration if kidney function is impaired. Premature neonates are particularly at risk because their kidneys are immature, and they require large amounts of calcium and phosphate solutions, which contain aluminum.

Research indicates that patients with impaired kidney function, including premature neonates, who receive parenteral levels of aluminum at greater than 4 to 5 mcg/kg/day accumulate aluminum at levels associated with central nervous system and bone toxicity. Tissue loading may occur at even lower rates of administration.

PRECAUTIONS

General

Do not use unless solution is clear and seal is intact.

Manganese 0.1 mg/mL (Manganese Chloride Injection, USP) should only be used in conjunction with a pharmacy directed admixture program using aseptic technique in a laminar flow environment; it should be used promptly and in a single operation without any repeated penetrations. Solution contains no preservatives; discard unused portion immediately after admixture procedure is completed.

Laboratory Tests

Serum manganese levels can be measured periodically at the discretion of the healthcare provider. Because of the low serum concentration normally present, samples will usually be analyzed by a reference laboratory.

Carcinogenesis, Mutagenesis, and Impairment of Fertility

Long-term animal studies to evaluate the carcinogenic potential of Manganese 0.1 mg/mL (Manganese Chloride Injection, USP) have not been performed, nor have studies been done to assess mutagenesis or impairment of fertility.

Nursing Mothers

It is not known whether this drug is excreted in human milk. Because many drugs are excreted in human milk, caution should be exercised when Manganese 0.1 mg/mL (Manganese Chloride Injection, USP) additive is administered to a nursing woman.

Pediatric Use

(See DOSAGE AND ADMINISTRATION section.) Safety and effectiveness in pediatric patients have not been established.

Pregnancy

Animal reproduction studies have not been conducted with manganese chloride. It is also not known whether manganese chloride can cause fetal harm when administered to a pregnant woman or can affect reproductive capacity. Manganese chloride should be given to a pregnant woman only if clearly indicated.

Geriatric Use

An evaluation of current literature revealed no clinical experience identifying differences in response between elderly and younger patients. In general, dose selection for an elderly patient should be cautious, usually starting at the low end of the dosing range, reflecting the greater frequency of decreased hepatic, renal, or cardiac function, and of concomitant disease or other drug therapy.

ADVERSE REACTIONS

None known.

DRUG ABUSE AND DEPENDENCE

None known.

OVERDOSAGE

Acute manganese toxicity was reported in adult patients following infusion of manganese more than 10,000-fold the recommended dosage and after use of dialysis fluid contaminated with manganese. Signs and symptoms included skin flushing, acute pancreatitis, elevated whole blood manganese concentrations, and MRI evidence of brain accumulation of manganese. Chronic infusion and oral intake of manganese above recommended dosage have resulted in neuropsychiatric symptoms and MRI evidence of brain accumulation of manganese (see WARNINGS).

DOSAGE AND ADMINISTRATION

Manganese 0.1 mg/mL (Manganese Chloride Injection, USP) contains 0.1 mg manganese/mL and is administered intravenously only after dilution. The additive should be administered in a volume of fluid at least 100 mL. For the adult receiving TPN, the suggested additive dosage for manganese is 55 mcg/day (0.55 mL/day).

Periodic monitoring of manganese plasma levels is suggested as a guideline for subsequent administration. (See WARNINGS.)

Parenteral products should be inspected visually for particulate matter and discoloration prior to administration, whenever solution and container permit. (See PRECAUTIONS.)

HOW SUPPLIED

Manganese 0.1 mg/mL (Manganese Chloride Injection, USP) is supplied in 10 mL Single-dose Plastic Vials.

Unit of Sale | Concentration
NDC 0409-4091-01 Tray of 25 Single-dose plastic vials | 1 mg/10 mL (0.1 mg/mL)

Store at 20 to 25°C (68 to 77°F) [See USP Controlled Room Temperature.]

Distributed by Hospira, Inc., Lake Forest, IL 60045 USA

LAB-1068-4.0

Revised: 12/2023

PRINCIPAL DISPLAY PANEL - 10 mL Vial Label

10 mL Vial
NDC 0409-4091-11

MANGANESE
1 mg/10 mL (0.1 mg/mL)

Manganese Chloride Inj., USP

FOR INTRAVENOUS USE ONLY AFTER DILUTION. Rx only

Distributed by Hospira, Inc., Lake Forest, IL 60045 USA

PRINCIPAL DISPLAY PANEL - 10 mL Vial Tray

10 mL Single-dose
NDC 0409-4091-01
Contains 25 of NDC 0409-4091-11
Rx only

Manganese
1 mg/10 mL (0.1 mg/mL)
Manganese Chloride Injection, USP

CAUTION: FOR INTRAVENOUS USE ONLY AFTER DILUTION.

Hospira